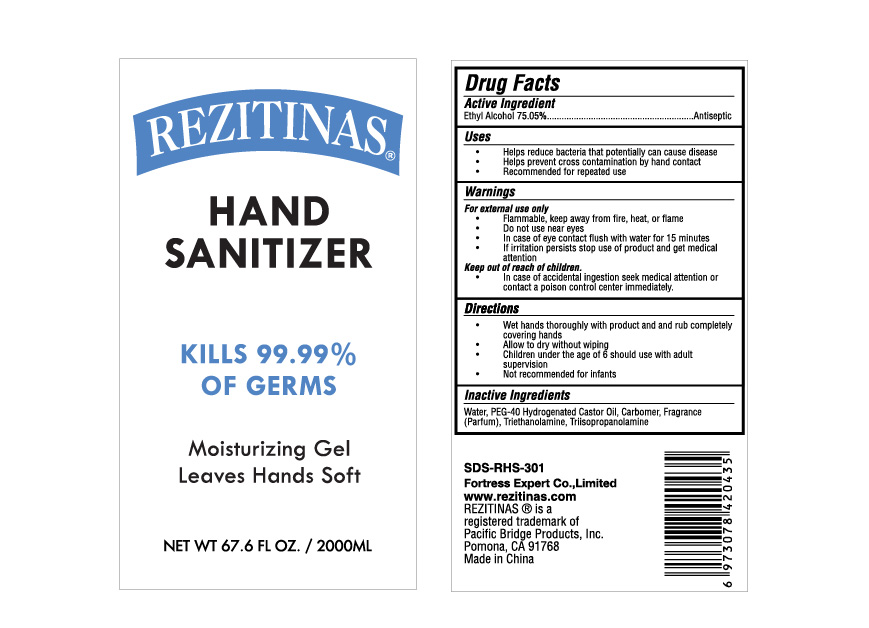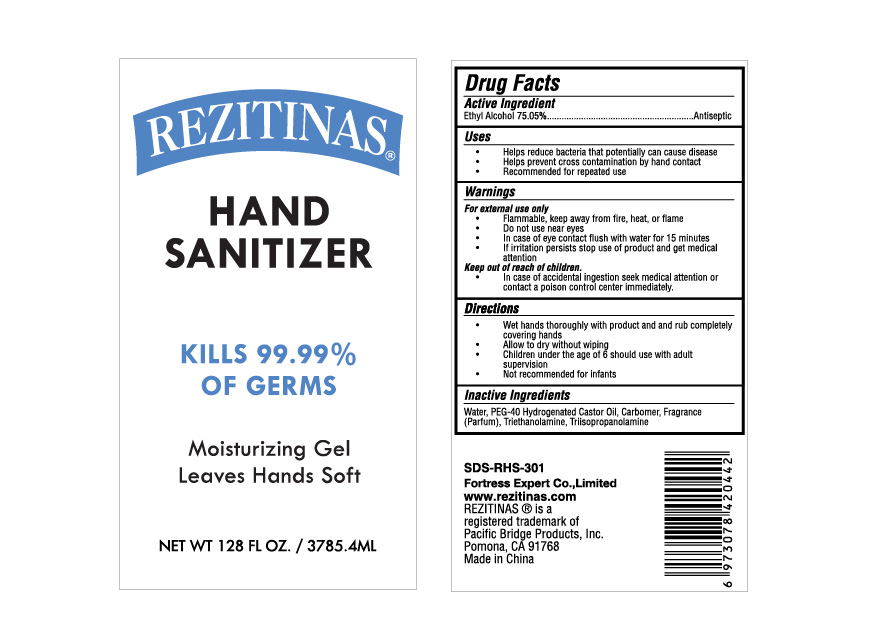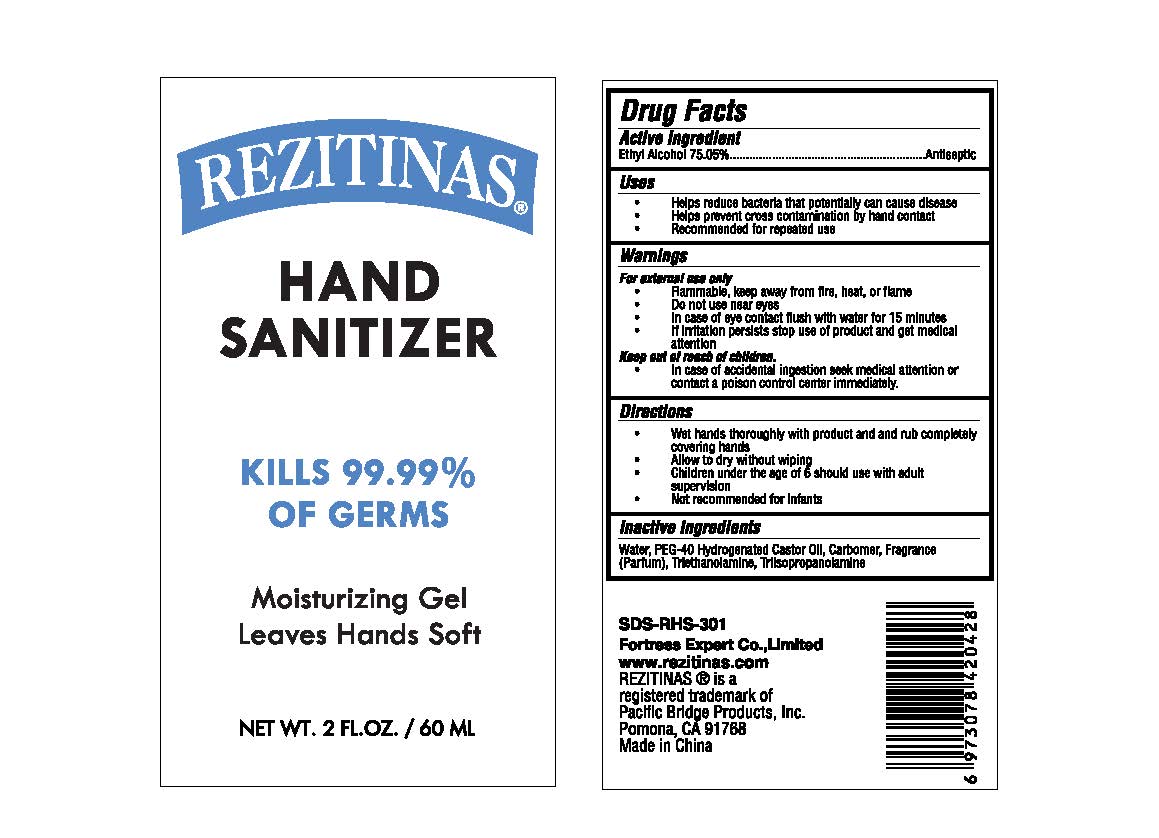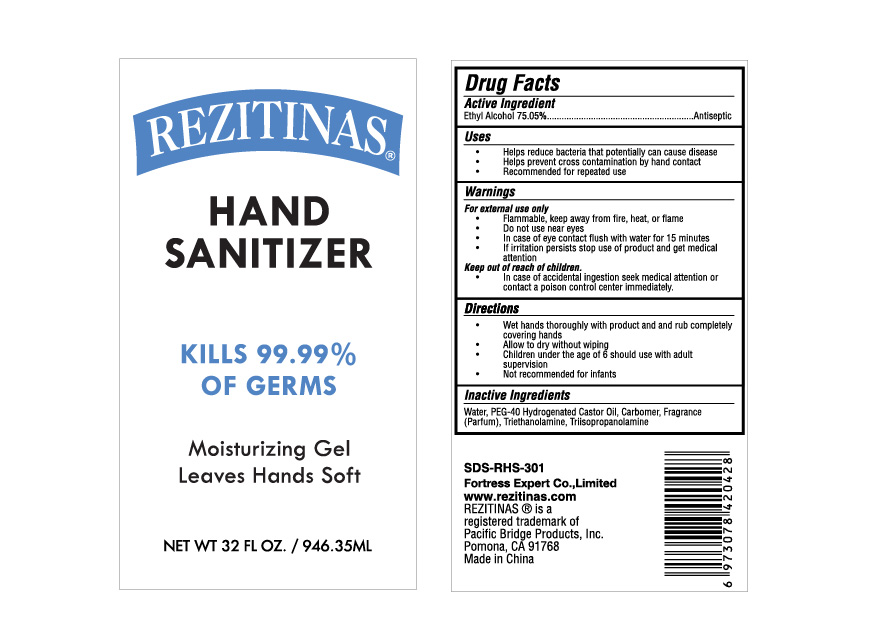 DRUG LABEL: HAND SANITIZER
NDC: 73549-005 | Form: GEL
Manufacturer: Fortress Expert Co., Ltd
Category: otc | Type: HUMAN OTC DRUG LABEL
Date: 20200610

ACTIVE INGREDIENTS: ALCOHOL 75.05 mL/100 mL
INACTIVE INGREDIENTS: FRAGRANCE LAVENDER & CHIA F-153480; TROLAMINE; POLYOXYL 40 HYDROGENATED CASTOR OIL; CARBOMER HOMOPOLYMER, UNSPECIFIED TYPE; WATER; TRIISOPROPANOLAMINE

HAND SANITIZER

Active Ingredient

Ethyl Alcohol 75.05%

Purpose

Antiseptic

Uses

Helps reduce bacteria that potentially can cause disease

Helps prevent cross contamination by hand contact

Recommended for repeated use

Warnings

For external use only

Flammable, keep away from fire, heat,or flame

Do not use near eyes

In case of eye contact flush with water for 15 minutes

if irritation persists stop use of product and get medical attention

Keep out of reach of children.

In case of accidental ingestion seek medical attention or contact a poison control center immediately.

Directions

Wet hands thoroughly with product and and rub completely covering hands

Allow to dry without wiping

Children under the age of 6 should use with adult

supervision

Not recommended for infants

Inactive Ingredients

Water, PEG-40 Hydrogenated Castor Oil, Carbomer,

Fragrance (Parfum), Triethanolamine, Triisopropanolamine